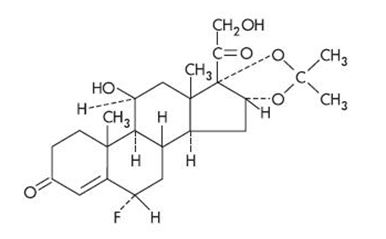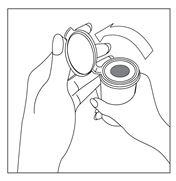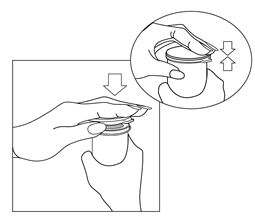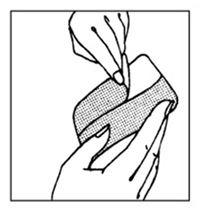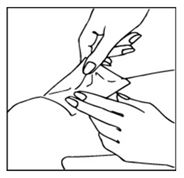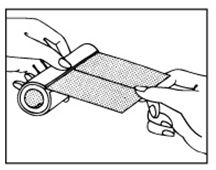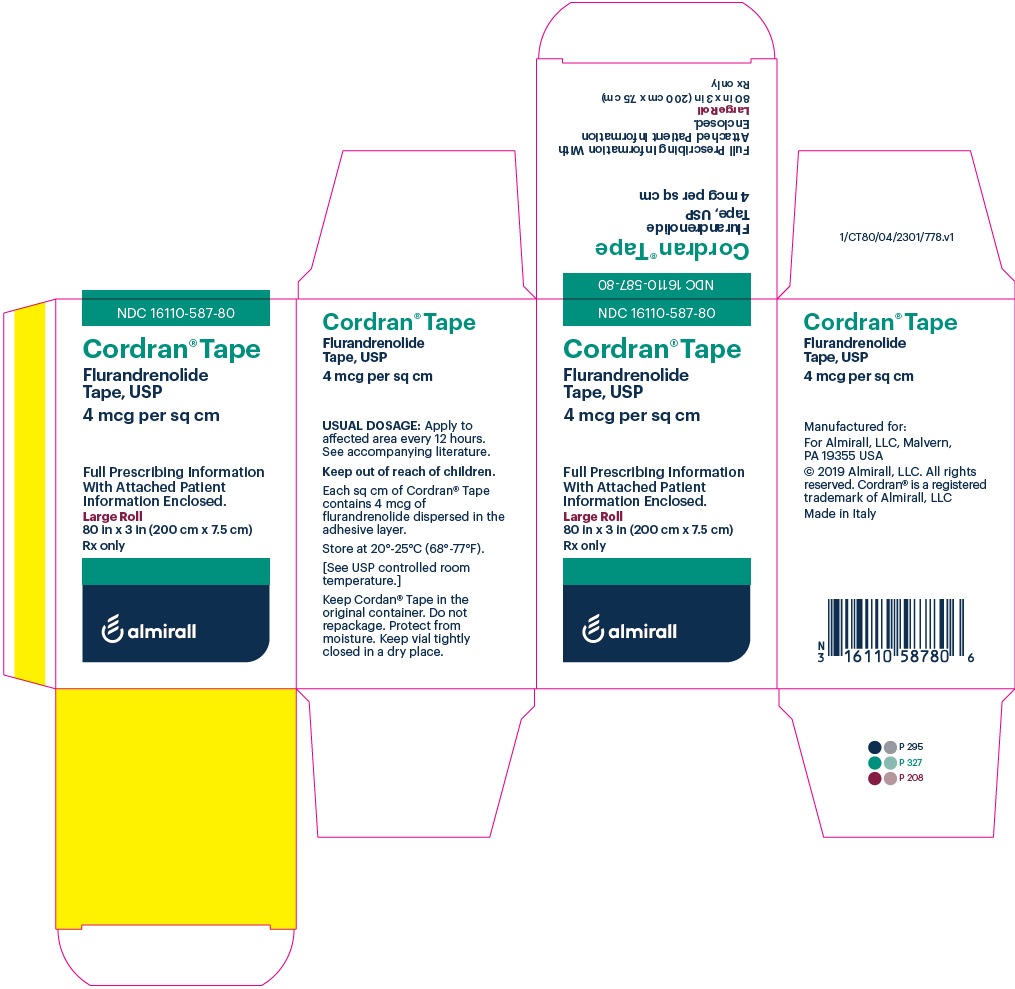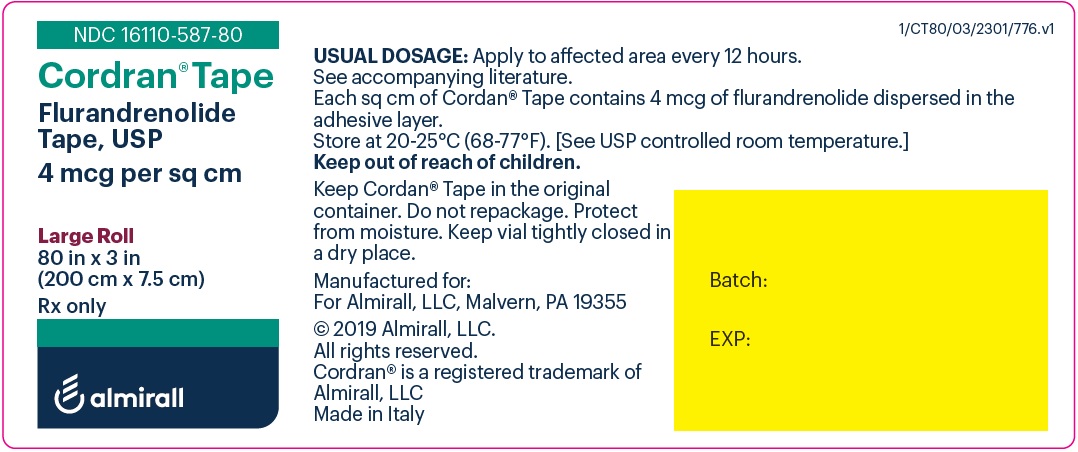 DRUG LABEL: CORDRAN
NDC: 16110-587 | Form: TAPE
Manufacturer: Almirall, LLC
Category: prescription | Type: HUMAN PRESCRIPTION DRUG LABEL
Date: 20250623

ACTIVE INGREDIENTS: Flurandrenolide 4 ug/1 cm2

Cordran® Tape
Flurandrenolide Tape, USP
Rx only

DESCRIPTION

Cordran Tape (Flurandrenolide Tape, USP) is a transparent, inconspicuous, plastic surgical tape. It contains Cordran (Flurandrenolide, USP), a potent corticosteroid for topical use. Flurandrenolide occurs as white to off-white, fluffy crystalline powder and is odorless. Flurandrenolide is practically insoluble in water and in ether. One gram dissolves in 72 mL of alcohol and in 10 mL of chloroform. The molecular weight of flurandrenolide is 436.52.

The chemical name of flurandrenolide is Pregn-4-ene-3,20-dione, 6-fluoro-11,21 dihydroxy-16,17-[(1-methylethylidene)bis(oxy)]-, (6α, 11ß, 16α)-; its empirical formula is C24H33FO6. The structural formula is as follows:

Each square centimeter contains 4 mcg (0.00916 μmol) flurandrenolide uniformly distributed in the adhesive layer. The tape is made of a thin, matte-finish polyethylene film that is slightly elastic and highly flexible.

The adhesive is a synthetic copolymer of acrylate ester and acrylic acid that is free from substances of plant origin. The pressure-sensitive adhesive surface is covered with a protective paper liner to permit handling and trimming before application.

CLINICAL PHARMACOLOGY

Cordran is primarily effective because of its anti-inflammatory, antipruritic, and vasoconstrictive actions.

The mechanism of the anti-inflammatory effect of topical corticosteroids is not completely understood. Various laboratory methods, including vasoconstrictor assays, are used to compare and predict potencies and/or clinical efficacies of the topical corticosteroids. There is some evidence to suggest that a recognizable correlation exists between vasoconstrictor potency and therapeutic efficacy in man. Corticosteroids with anti-inflammatory activity may stabilize cellular and lysosomal membranes. There is also the suggestion that the effect on the membranes of lysosomes prevents the release of proteolytic enzymes and, thus, plays a part in reducing inflammation.

The tape serves as both a vehicle and an occlusive dressing. Retention of insensible perspiration by the tape results in hydration of the stratum corneum and improved diffusion of the medication. The skin is protected from scratching, rubbing, desiccation, and chemical irritation. The tape acts as a mechanical splint to fissured skin. Since it prevents removal of the medication by washing or the rubbing action of clothing, the tape formulation provides a sustained action.

Pharmacokinetics—The extent of percutaneous absorption of topical corticosteroids is determined by many factors, including the vehicle, the integrity of the epidermal barrier, and the use of occlusive dressings.

Topical corticosteroids can be absorbed from normal intact skin. Inflammation and/or other disease processes in the skin increase percutaneous absorption. Occlusive dressings substantially increase the percutaneous absorption of topical corticosteroids. Thus, occlusive dressings may be a valuable therapeutic adjunct for treatment of resistant dermatoses (see DOSAGE AND ADMINISTRATION).

Once absorbed through the skin, topical corticosteroids are handled through pharmacokinetic pathways similar to those of systemically administered corticosteroids. Corticosteroids are bound to plasma proteins in varying degrees. They are metabolized primarily in the liver and then excreted in the kidneys. Some of the topical corticosteroids and their metabolites are also excreted into the bile.

INDICATIONS AND USAGE

For relief of the inflammatory and pruritic manifestations of corticosteroid-responsive dermatoses, particularly dry, scaling localized lesions.

CONTRAINDICATIONS

Topical corticosteroids are contraindicated in patients with a history of hypersensitivity to any of the components of these preparations.

Use of Cordran Tape is not recommended for lesions exuding serum or in intertriginous areas.

PRECAUTIONS

General -

Systemic absorption of topical corticosteroids has produced reversible hypothalamic-pituitary-adrenal (HPA) axis suppression, manifestations of Cushing’s syndrome, hyperglycemia, and glucosuria in some patients.

Conditions that augment systemic absorption include application of the more potent steroids, use over large surface areas, prolonged use, and the addition of occlusive dressings.

Therefore, patients receiving a large dose of a potent topical steroid applied to a large surface area or under an occlusive dressing should be evaluated periodically for evidence of HPA axis suppression by using urinary-free cortisol and ACTH stimulation tests. If HPA axis suppression is noted, an attempt should be made to withdraw the drug, to reduce the frequency of application, or to substitute a less potent steroid.

Recovery of HPA axis function is generally prompt and complete on discontinuation of the drug. Infrequently, signs and symptoms of steroid withdrawal may occur, so that supplemental systemic corticosteroids are required.

Pediatric patients may absorb proportionately larger amounts of topical corticosteroids and thus be more susceptible to systemic toxicity (see Pediatric Use under PRECAUTIONS).

If irritation develops, topical corticosteroids should be discontinued and appropriate therapy instituted.

In the presence of dermatologic infections, the use of an appropriate antifungal or antibacterial agent should be instituted. If a favorable response does not occur promptly, Cordran should be discontinued until the infection has been adequately controlled.

Information for the Patient -

Patients using topical corticosteroids should receive the following information and instructions:

- This medication is to be used as directed by the physician. It is for external use only. Avoid contact with the eyes.
- Patients should be advised not to use this medication for any disorder other than that for which it was prescribed.
- The treated skin area should not be bandaged or otherwise covered or wrapped in order to be occlusive unless the patient is directed to do so by the physician.
- Patients should report any signs of local adverse reactions, especially under occlusive dressing.
- Parents of pediatric patients should be advised not to use tight-fitting diapers or plastic pants on a patient being treated in the diaper area, because these garments may constitute occlusive dressings.

Laboratory Tests -

The following tests may be helpful in evaluating the HPA axis suppression:

Urinary-free cortisol test
ACTH stimulation test

Carcinogenesis, Mutagenesis, and Impairment of Fertility -

Long-term animal studies have not been performed to evaluate the carcinogenic potential or the effect on fertility of topical corticosteroids.

Studies to determine mutagenicity with prednisolone and hydrocortisone have revealed negative results.

Usage in Pregnancy -

Corticosteroids are generally teratogenic in laboratory animals when administered systemically at relatively low dosage levels. The more potent corticosteroids have been shown to be teratogenic after dermal application in laboratory animals. There are no adequate and well-controlled studies in pregnant women on teratogenic effects from topically applied corticosteroids. Therefore, topical corticosteroids should be used during pregnancy only if the potential benefit justifies the potential risk to the fetus. Drugs of this class should not be used extensively for pregnant patients or in large amounts or for prolonged periods of time.

Nursing Mothers -

It is not known whether topical administration of corticosteroids could result in sufficient systemic absorption to produce detectable quantities in breast milk. Systemically administered corticosteroids are secreted into breast milk in quantities not likely to have a deleterious effect on the infant. Nevertheless, caution should be exercised when topical corticosteroids are administered to a nursing woman.

Pediatric Use -

Pediatric patients may demonstrate greater susceptibility to topical-corticosteroid-induced HPA axis suppression and Cushing’s syndrome than do mature patients because of a larger skin surface area to body weight ratio.

Hypothalamic-pituitary-adrenal (HPA) axis suppression, Cushing’s syndrome, and intracranial hypertension have been reported in pediatric patients receiving topical corticosteroids. Manifestations of adrenal suppression in pediatric patients include linear growth retardation, delayed weight gain, low plasma-cortisol levels, and absence of response to ACTH stimulation. Manifestations of intracranial hypertension include bulging fontanelles, headaches, and bilateral papilledema.

Administration of topical corticosteroids to pediatric patients should be limited to the least amount compatible with an effective therapeutic regimen. Chronic corticosteroid therapy may interfere with the growth and development of pediatric patients.

ADVERSE REACTIONS

The following local adverse reactions are reported infrequently with topical corticosteroids but may occur more frequently with the use of occlusive dressings. These reactions are listed in an approximate decreasing order of occurrence: burning, itching, irritation, dryness, folliculitis, hypertrichosis, acneiform eruptions, hypopigmentation, perioral dermatitis, allergic contact dermatitis.

The following may occur more frequently with occlusive dressings: maceration of the skin, secondary infection, skin atrophy, striae, miliaria.

OVERDOSAGE

Topically applied corticosteroids can be absorbed in sufficient amounts to produce systemic effects (see PRECAUTIONS).

DOSAGE AND ADMINISTRATION

Occlusive dressings may be used for the management of psoriasis or recalcitrant conditions.

If an infection develops, the use of Cordran Tape and other occlusive dressings should be discontinued and appropriate antimicrobial therapy instituted.

Replacement of the tape every 12 hours produces the lowest incidence of adverse reactions, but it may be left in place for 24 hours if it is well tolerated and adheres satisfactorily. When necessary, the tape may be used at night only and removed during the day.

If ends of the tape loosen prematurely, they may be trimmed off and replaced with fresh tape.

The directions given below are included for the patient to follow unless otherwise instructed by the physician.

APPLICATION OF CORDRAN TAPE

IMPORTANT: Skin should be clean and dry before tape is applied. Tape should always be cut, never torn.

DIRECTIONS FOR USE:

- Prepare skin as directed by your physician or as follows: Gently clean the area to be covered to remove scales, crusts, dried exudates, and any previously used ointments or creams. A germicidal soap or cleanser should be used to prevent the development of odor under the tape. Shave or clip the hair in the treatment area to allow both good contact with the skin and comfortable removal. If shower or tub bath is to be taken, it should be completed before the tape is applied. The skin should be dry before application of the tape.
- Remove tape from flip-top vial and cut a piece slightly larger than area to be covered. Round off corners.
- Return remainder of tape roll to vial and tightly close the lid.
- Pull white paper from transparent tape. Be careful that tape does not stick to itself.
- Apply tape, keeping skin smooth; press tape into place.

Keep Cordran Tape in the original container. Do not repackage. Protect from moisture. Keep vial tightly closed in a dry place.

REPLACEMENT OF TAPE:

Unless instructed otherwise by your physician, replace tape after 12 hours. Cleanse skin and allow it to dry for 1 hour before applying new tape.

IF IRRITATION OR INFECTION DEVELOPS, REMOVE TAPE AND CONSULT PHYSICIAN.

HOW SUPPLIED

Tape:

4 mcg/sq cm—small roll, 24 in x 3 in (60 cm x 7.5 cm), in a flip-top vial
NDC 16110-587-24

4 mcg/sq cm—large roll, 80 in x 3 in (200 cm x 7.5 cm), in a flip-top vial
NDC 16110-587-80

Store at 20-25°C (68-77°F). [See USP controlled room temperature.]

Keep out of reach of children.

Rx only

REFERENCES

Bard JW: Flurandrenolide tape in the treatment of lichen simplex chronicus. J Ky Med Assoc 1969;67:668.

Baxter DL, Stoughton RB: Mitotic index of psoriatic lesions treated with anthralin, glucocorticosteroid and occlusion only. J Invest Dermatol 1970;54:410.

Compilation of clinical reports on Cordran Tape received by Eli Lilly and Company.

Halprin KM, Fukui K, Ohkawara A: Flurandrenolone (Cordran) tape and carbohydrate metabolizing enzymes. Arch Dermatol 1969;100:336.

Labow TA, Eisert J, Sanders SL: Flurandrenolide tape in treatment of psoriasis. NY State J Med 1969;69:3138.

Ronchese F: Flurandrenolone tape therapy. RI Med J 1969;52:389.

Sellers FM: Investigative study of flurandrenolone tape in a series of ambulatory outpatients. J Indiana State Med Assoc 1970;63:34.

Weiner MA: Flurandrenolone tape, a new preparation for occlusive therapy, J Invest Dermatol 1966; 47:63.

Manufactured for:
Almirall, LLC
Malvern, PA 19355

© 2019 Almirall, LLC. All rights reserved.
Cordran® is a registered trademark of Almirall, LLC.

Content Updated: June 2022

For the Patient

Cordran® Tape

Flurandrenolide Tape, USP

DIRECTIONS FOR USE

APPLICATION OF MEDICATED TRANSPARENT TAPE

Rx only

IMPORTANT: Skin should be clean and dry before tape is applied. Tape should always be cut, never torn.

- Prepare skin as directed by your physician or as follows: Gently clean the area to be covered to remove scales, crusts, dried exudates, and any previously used ointments or creams. A germicidal soap or cleanser should be used to prevent the development of odor under the tape. Shave or clip the hair in the treatment area to allow both good contact with the skin and comfortable removal. If a shower or tub bath is to be taken, it should be completed before the tape is applied. The skin should be dry before application of the tape.
- Remove tape from flip-top vial and cut a piece slightly larger than area to be covered. Round off corners.
- Return remainder of tape roll to vial and tightly close the lid.
- Pull white paper backing from transparent tape. Be careful that tape does not stick to itself.
  - Apply tape, keeping skin smooth; press tape into place.

REPLACEMENT OF TAPE

Unless instructed otherwise by your physician, replace tape after 12 hours. Cleanse skin and allow it to dry for 1 hour before applying new tape.

DISPENSING THE TAPE

To use the roll as a dispenser, pull the tape as illustrated.

IF IRRITATION OR INFECTION DEVELOPS, REMOVE TAPE AND CONSULT PHYSICIAN.

Store at 20 - 25℃ (68 - 77℉). [See USP controlled room temperature.]

Keep Cordran Tape in the original container. Do not repackage. Protect from moisture. Keep vial tightly closed in a dry place.

Keep out of reach of children.

Rx only

Manufactured for:
Almirall, LLC
Malvern, PA 19355

© 2019 Almirall, LLC. All rights reserved.

Cordran® is a registered trademark of Almirall, LLC.

almirall

Content Updated: June 2022